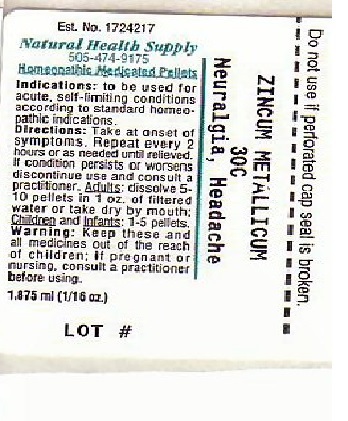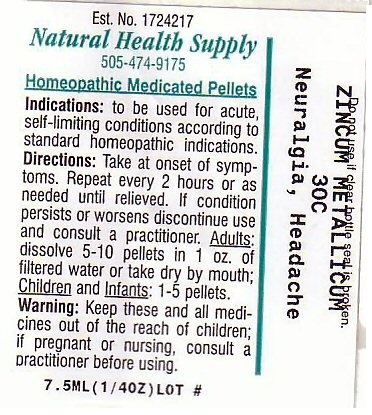 DRUG LABEL: NEURALGIA HEADACHE
NDC: 64117-052 | Form: PELLET
Manufacturer: Natural Health Supply
Category: homeopathic | Type: HUMAN OTC DRUG LABEL
Date: 20201201

ACTIVE INGREDIENTS: ZINC 30 [hp_C]/1 mL
INACTIVE INGREDIENTS: LACTOSE; SUCROSE

NEURALGIA HEADACHE

Drug Facts

Active Ingredient

ZINCUM METALLICUM

Purpose: Neuralgia Headache

INDICATIONS AND USAGE

Indications: To be used for acute self-limiting conditions according to standard homeopathic indications

Warnings:

If pregnant or nursing, consult a practitioner before using.

Keep out of reach of children.

Inactive Ingredients: Lactose, Sucrose

PACKAGE LABEL

Est. No. 1724217

Natural Health Supply

505-474-9175

Homeopathic Medicated Pellets

Do not use if clear bottle seal is broken

ZINCUM METALLICUM 30C

Neuralgia Headache

Lot #__________________